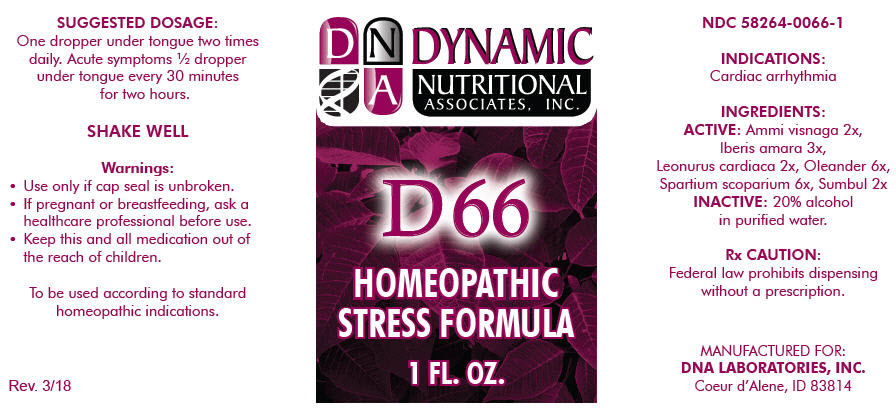 DRUG LABEL: D-66
NDC: 58264-0066 | Form: SOLUTION
Manufacturer: DNA Labs, Inc.
Category: homeopathic | Type: HUMAN OTC DRUG LABEL
Date: 20250113

ACTIVE INGREDIENTS: VISNAGA DAUCOIDES FRUIT 2 [hp_X]/1 mL; IBERIS AMARA SEED 3 [hp_X]/1 mL; LEONURUS CARDIACA 2 [hp_X]/1 mL; NERIUM OLEANDER LEAF 6 [hp_X]/1 mL; CYTISUS SCOPARIUS WHOLE 6 [hp_X]/1 mL; FERULA SUMBUL ROOT 2 [hp_X]/1 mL
INACTIVE INGREDIENTS: ALCOHOL; WATER

D-66

NDC 58264-0066-1

INDICATIONS

PURPOSE

Cardiac arrhythmia

INGREDIENTS

ACTIVE

Ammi visnaga 2x, lberis amara 3x, Leonurus cardiaca 2x, Oleander 6x, Spartium scoparium 6x, Sumbul 2x

INACTIVE

20% alcohol in purified water.

Rx CAUTION

Federal law prohibits dispensing without a prescription.

SUGGESTED DOSAGE

One dropper under tongue two times daily. Acute symptoms ½ dropper under tongue every 30 minutes for two hours.

STORAGE AND HANDLING

SHAKE WELL

Warnings

- Use only if cap seal is unbroken.

PREGNANCY OR BREAST FEEDING

- If pregnant or breastfeeding, ask a healthcare professional before use.

KEEP OUT OF REACH OF CHILDREN

- Keep this and all medication out of the reach of children.

To be used according to standard homeopathic indications.

PRINCIPAL DISPLAY PANEL - 1 FL. OZ. Bottle Label

DYNAMIC
NUTRITIONAL
ASSOCIATES, INC.

D 66

HOMEOPATHIC
STRESS FORMULA

1 FL. OZ.